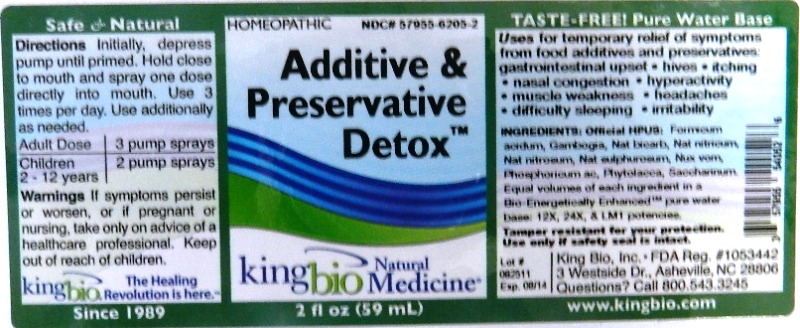 DRUG LABEL: Additive and Preservative Detox
NDC: 57955-6205 | Form: LIQUID
Manufacturer: King Bio Inc.
Category: homeopathic | Type: HUMAN OTC DRUG LABEL
Date: 20111116

ACTIVE INGREDIENTS: FORMIC ACID 12 [hp_X]/59 mL; GAMBOGE 12 [hp_X]/59 mL; SODIUM BICARBONATE 12 [hp_X]/59 mL; SODIUM NITRATE 12 [hp_X]/59 mL; SODIUM NITRITE 12 [hp_X]/59 mL; SODIUM SULFITE 12 [hp_X]/59 mL; STRYCHNOS NUX-VOMICA SEED 12 [hp_X]/59 mL; PHOSPHORIC ACID 12 mL/59 mL; PHYTOLACCA AMERICANA ROOT 12 mL/59 mL; SACCHARIN 12 [hp_X]/59 mL
INACTIVE INGREDIENTS: WATER

Additive and Preservative Detox

Active Ingredients

Ingredients: Official HPUS:

Formicum Acidum

Gambogia

Natrum Bicarbonicum

Natrum Nitricum

Natrum Nitrosum

Natrum Sulphurosum

Nux Vomica

Phosphoricum Acidum

Phytolacca Decandra

Saccharinum

Reference image detox.jpg

Inactive Ingredient

Equal volumes of each ingredient in a Bio-Energetically Enhanced pure water base:12X, 24X and LM1 Potencies.

Reference image detox.jpg

Purpose

Uses for temporary relief of symptoms from food additives and preservatives:

- gastrointestinal upset
- hives
- itching
- nasal congestion
- hyperactivity
- muscle weakness
- headaches
- difficulty sleeping
- irritability

Reference image detox.jpg

Dosage and Administration

Directions Initially, depress pump until primed. Hold close to mouth and spray one dose directly into mouth. Use 3 times per day. Use additionally as needed.

Adult Dose: 3 pump sprays

Children 2 - 12 years: 2 pump sprays

Reference image detox.jpg

Warnings

If symptoms persist or worsen, or if pregnant or nursing, take only on advice of a healthcare professional. Keep out of reach of children.

Reference image detox.jpg

Keep Out Of Reach Of Children

Reference image detox.jpg

Indications and usage

Uses for temporary relief of symptoms from food additives and preservatives: gastrointestinal upset, hives, itching, nasal congestion, hyperactivity, muscle weakness, headaches, difficulty sleeping, irritability.

Reference image detox.jpg

PACKAGE LABEL

King Bio Inc.

3 Westside Drive

Asheville, NC 28806

Questions? Call 800.543.3245

www.kingbio.com